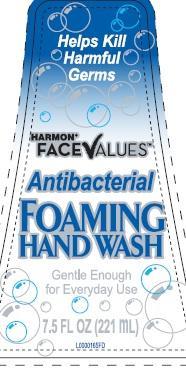 DRUG LABEL: Hand Wash
NDC: 63940-641 | Form: LIQUID
Manufacturer: Harmon Stores, Inc
Category: otc | Type: HUMAN OTC DRUG LABEL
Date: 20140605

ACTIVE INGREDIENTS: BENZALKONIUM CHLORIDE .999 mg/1 mL
INACTIVE INGREDIENTS: WATER; GLYCERIN; CETRIMONIUM CHLORIDE; COCO MONOETHANOLAMIDE; LAURAMIDOPROPYLAMINE OXIDE; MYRISTAMIDOPROPYLAMINE OXIDE; PEG-120 METHYL GLUCOSE DIOLEATE; CITRIC ACID MONOHYDRATE; EDETATE SODIUM; METHYLCHLOROISOTHIAZOLINONE; METHYLISOTHIAZOLINONE; FD&C YELLOW NO. 5; FD&C RED NO. 4

Drug Facts

Active ingredient

Benzalkonium chloride 0.10%

purpose

Antibacterial

Use

for handwashing to decrease bacteria on the skin

warnings

For external use only-hands only

When using this product

- avoid contact with eyes. If contact occurs, rinse eyes thoroughly with water.

Stop use and ask a doctor if

- irritation or redness develops
- condition persists for more than 72 hours

Keep out of reach of children

if swallowed, get medical help or contact a Poison Control Center right away.

Directions

- wet hands
- apply palmful to hands
- scrub thoroughly
- rinse thoroughly

Inactive ingredients

water, glycerin, cetrimonium chloride, cocamide MEA, lauramidopropylamine oxide, myristamidopropylamine oxide, PEG-120 methyl glucose dioleate, fragrance, citric acid, tetrasodium EDTA, methylchloroisothiazolinone, methylisothiazolinone, yellow 5, red 4

claims

REFILL ONLY WITH FOAMING HAND SOAP, REGULAR LIQUID HAND SOAP WILL NOT FOAM

Adverse reactions

Distributed by Harmon Stores, Inc.

650 Liberty Ave., Union, NJ 07083 USA

Harmon Stores, Inc.

Visit us at: www.facevalues.com

Principal Display Panel

Helps Kill

Harmful

Germs

HARMON

FACEVALUES

Antibacterial

FOAMING

HAND WASH

Gentle Enough

for Everyday Use

7.5 FL OZ (221 mL)